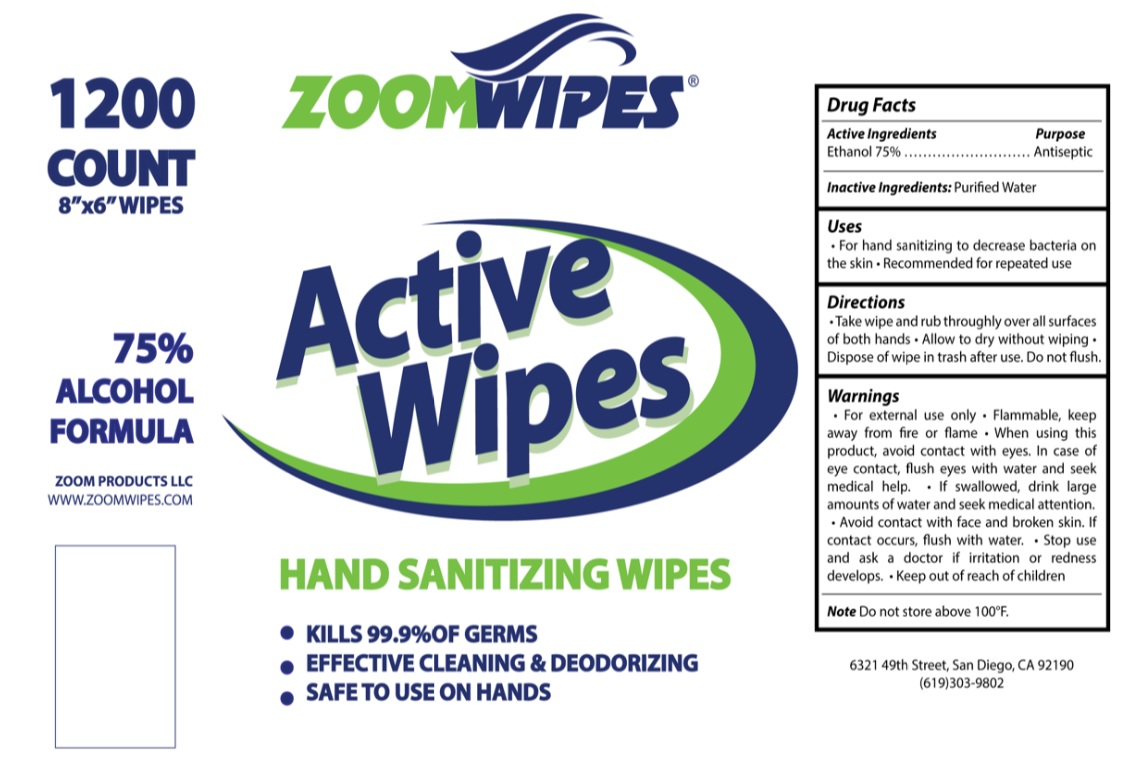 DRUG LABEL: ZOOM ACTIVE ALCOHOL WIPES
NDC: 70401-300 | Form: CLOTH
Manufacturer: Zoom Products, Llc.
Category: otc | Type: HUMAN OTC DRUG LABEL
Date: 20200901

ACTIVE INGREDIENTS: ALCOHOL 75 mL/100 mL
INACTIVE INGREDIENTS: WATER

ZOOMWIPES® Active Wipes HAND SANITIZING WIPES

Active Ingredients

Ethanol 75%

Purpose

Antiseptic

Inactive Ingredients: Purified Water

Uses

• For hand sanitizing to decrease bacteria on the skin • Recommended for repeated use

Directions

• Take wipe and rub thoroughly over all surfaces of both hands. • Allow to dry without wiping. • Dispose of wipe in trash after use. Do not flush.

Warnings

• For external use only • Flammable, keep away from fire or flame • When using this product, avoid contact with eyes. In case of eye contact, flush eyes with water and seek medical help. • If swallowed, drink large amounts of water and seek medical attention. • Avoid contact with face and broken skin. If contact occurs, flush with water. • Stop use and ask a doctor if irritation or redness develops.

• Keep out of reach of children

STORAGE AND HANDLING

Note Do not store above 100°F

• KILLS 99.9% OF GERMS

• EFFECTIVE CLEANING & DEODORIZING

• SAFE TO USE ON HANDS

75% ALCOHOL FORMULA

ZOOM PRODUCTS LLC

WWW.ZOOMWIPES.COM

6321 49th Street, San Diego, CA 92190

(619)303-9802